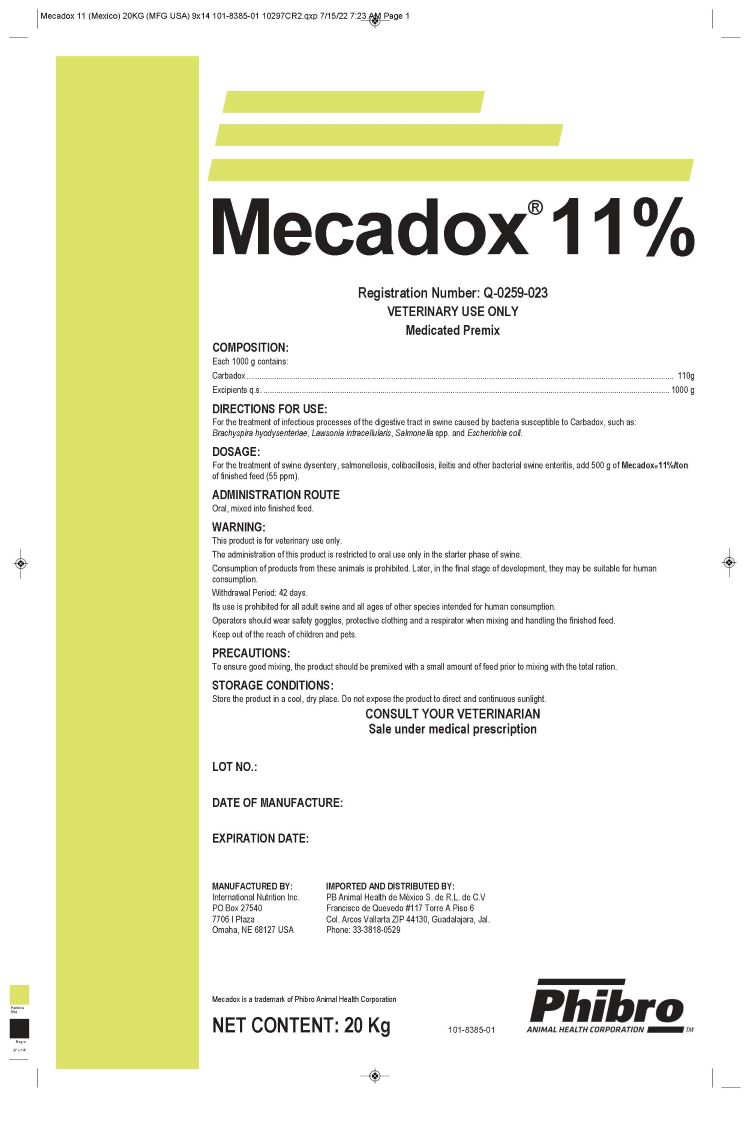 DRUG LABEL: Mecadox 11%
NDC: 66104-4955 | Form: POWDER
Manufacturer: Phibro Animal Health
Category: animal | Type: OTC ANIMAL DRUG LABEL
Date: 20250425

ACTIVE INGREDIENTS: CARBADOX 110 kg/110 kg

Mecadox 11%

DOSAGE AND ADMINISTRATION

DOSAGE:

For the treatment of swine dysentery, salmonellosis, colibacillosis, ileitis and other bacterial swine enteritis, add 500 g of Mecadox® 11%/ton of finished feed (55 ppm).

ADMINISTRATION ROUTE

Oral, mixed into finished feed.

PRECAUTIONS:

To ensure good mixing, the product should be premixed with a small amount of feed prior to mixing with the total ration.

WARNING:

This product is for veterinary use only.
The administration of this product is restricted to oral use only in the starter phase of swine.
Consumption of products from these animals is prohibited. Later, in the final stage of development, they may be suitable for human consumption.
Withdrawal Period: 42 days.
Its use is prohibited for all adult swine and all ages of other species intended for human consumption.
Operators should wear safety goggles, protective clothing and a respirator when mixing and handling the finished feed.
Keep out of the reach of children and pets.

STORAGE CONDITIONS:

Store the product in a cool, dry place. Do not expose the product to direct and continuous sunlight.

DIRECTIONS FOR USE:

For the treatment of infectious processes of the digestive tract in swine caused by bacteria susceptible to Carbadox, such as:
Brachyspira hyodysenteriae, Lawsonia intracellularis, Salmonella spp. and Escherichia coli.

Label

CONSULT YOUR VETERINARIAN
Sale under medical prescription
LOT NO.:
DATE OF MANUFACTURE: EXPIRATION DATE: